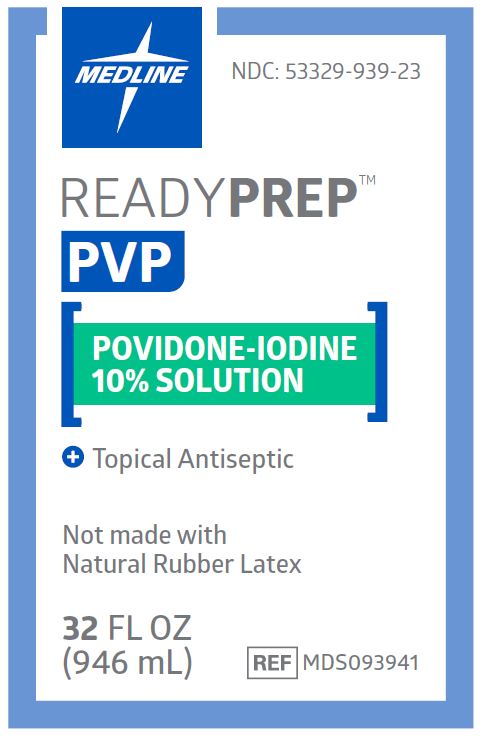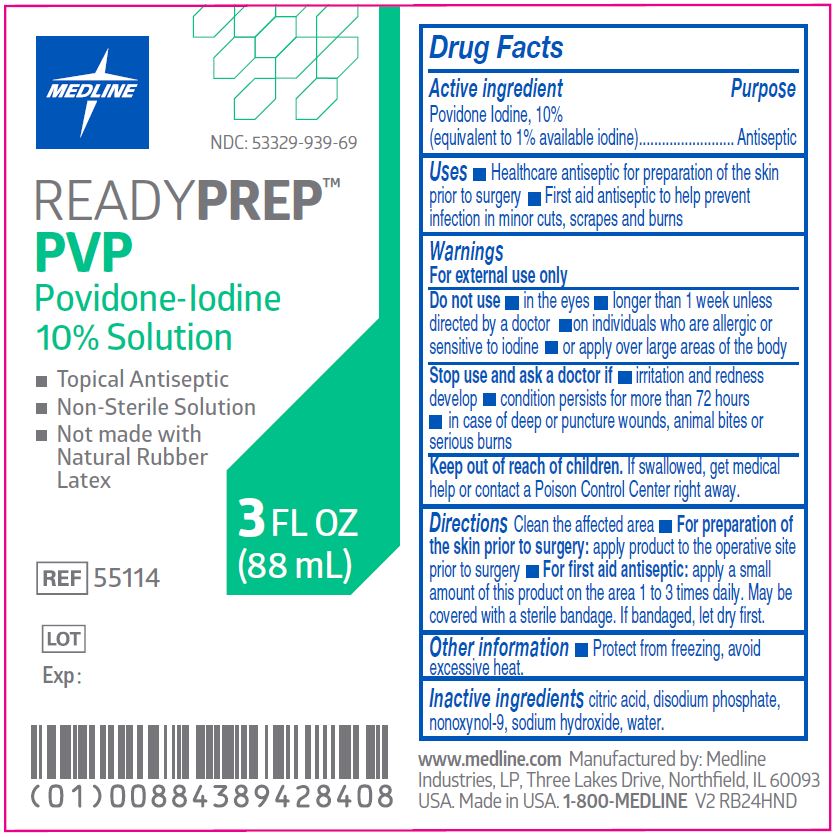 DRUG LABEL: Povidone-Iodine
NDC: 53329-939 | Form: SOLUTION
Manufacturer: Medline Industries, LP
Category: otc | Type: HUMAN OTC DRUG LABEL
Date: 20240301

ACTIVE INGREDIENTS: POVIDONE-IODINE 10 mg/1 mL
INACTIVE INGREDIENTS: CITRIC ACID MONOHYDRATE; SODIUM PHOSPHATE, DIBASIC, DIHYDRATE; NONOXYNOL-9; SODIUM HYDROXIDE; WATER

939 PVP Prep Solution

Active ingredient

Povidone Iodine 10%

(equivalent to 1% available iodine)

Purpose

Antiseptic

Uses

- healthcare antiseptic for preparation of the skin prior to surgery
- first aid antiseptic to help prevent infection in minor cuts, scrapes and burns

Warnings

For external use only.

Do not use

- in the eyes
- longer than 1 week unless directed by a doctor
- on individuals who are allergic or sensitive to iodine
- or apply over large areas of the body

Stop use and ask a doctor if

- irritation and redness develop
- condition persists for more than 72 hours
- in case of deep or puncture wounds, animal bites or serious burns

Keep out of reach of children.

If swallowed, get medical help or contact a Poison Control Center right away.

Directions

Clean the affected area.

- For preparation of the skin prior to surgery: apply product to the operative site prior to surgery
- For first aid antiseptic: apply a small amount of this product on the area 1 to 3 times daily. May be covered with a sterile bandage. If bandaged, let dry first.

Other information

- protect from freezing, avoid excessive heat

Inactive ingredients

citric acid, disodium phosphate, nonoxynol-9, sodium hydroxide, water

Manufacturing Information

Manufactured by:

Medline Industries, LP

Three Lakes Drive, Northifeld, IL 60093 USA

Made in USA

www.medline.com

1-800-MEDLINE (633-5463)

REF: MDS093941

V1 RB22DYN

REF: 55114
V2 RB24HND